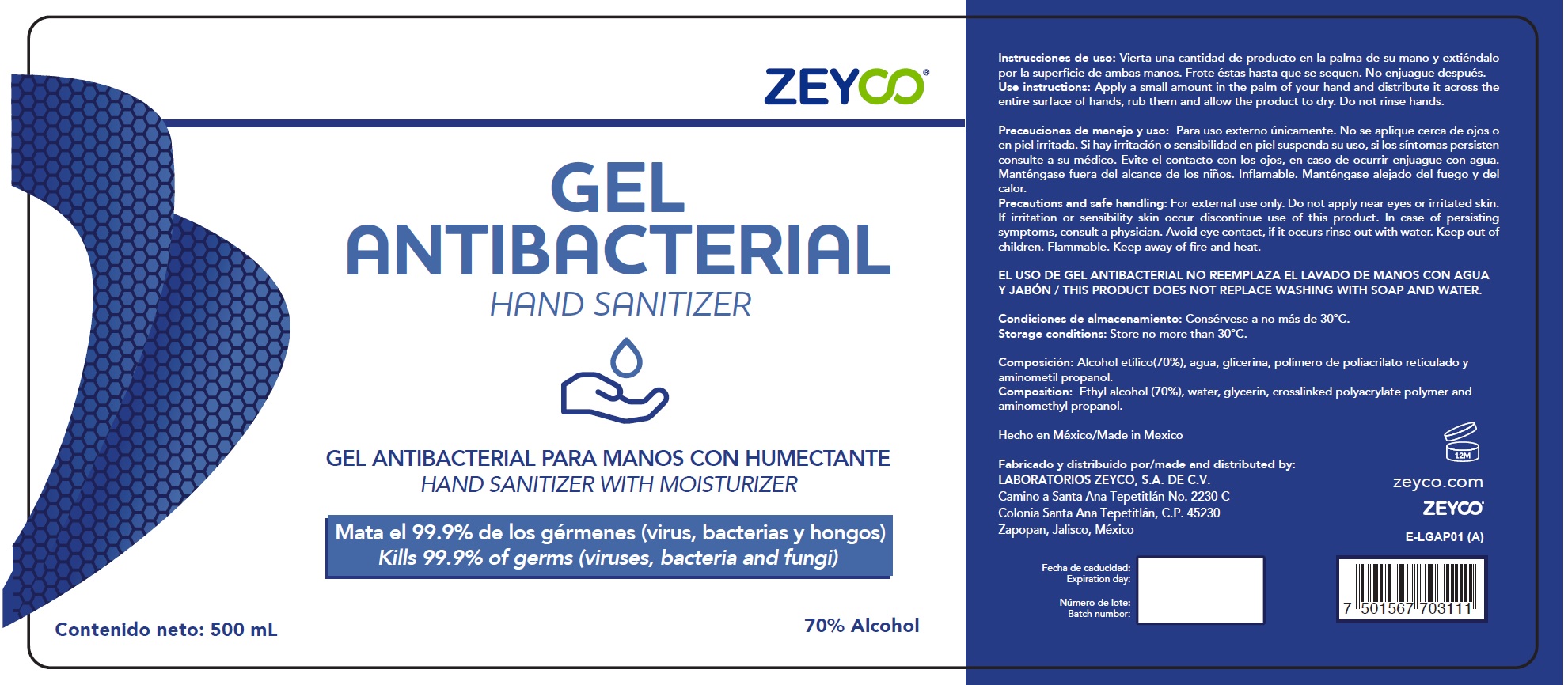 DRUG LABEL: Antibacterial Hand Sanitizer
NDC: 63710-001 | Form: GEL
Manufacturer: Laboratorios Zeyco, S.A. de C.V.
Category: otc | Type: HUMAN OTC DRUG LABEL
Date: 20231026

ACTIVE INGREDIENTS: ALCOHOL 0.7 mL/1 mL
INACTIVE INGREDIENTS: WATER; GLYCERIN; AMINOMETHYLPROPANOL

Gel Antibacterial Hand Sanitizer

Use instructions:

Apply a small amount in the palm of your hand and distribute it across the entire surface of hands, rub them and allow the product to dry. Do not rinse hands.

Use instructions:

Apply a small amount in the palm of your hand and distribute it across the entire surface of hands, rub them and allow the product to dry. Do not rinse hands.

Precautions and safe handling:

For external use only.

Do not apply near eyes or irritated skin.

STOP USE

If irritation or sensibility skin occur discontinue use of this product. In case of persisting symptoms, consult a physician. Avoid eye contact, if it occurs rinse out with water.

KEEP OUT OF REACH OF CHILDREN

Keep out of children. Flammable. Keep away of fire and heat.

Storage conditions:

Store no more than 30°C.

Composition:

Ethyl alcohol (70%)

INACTIVE INGREDIENT

water, glycerin, crosslinked polyacrylate polymer and aminomethyl propanol.